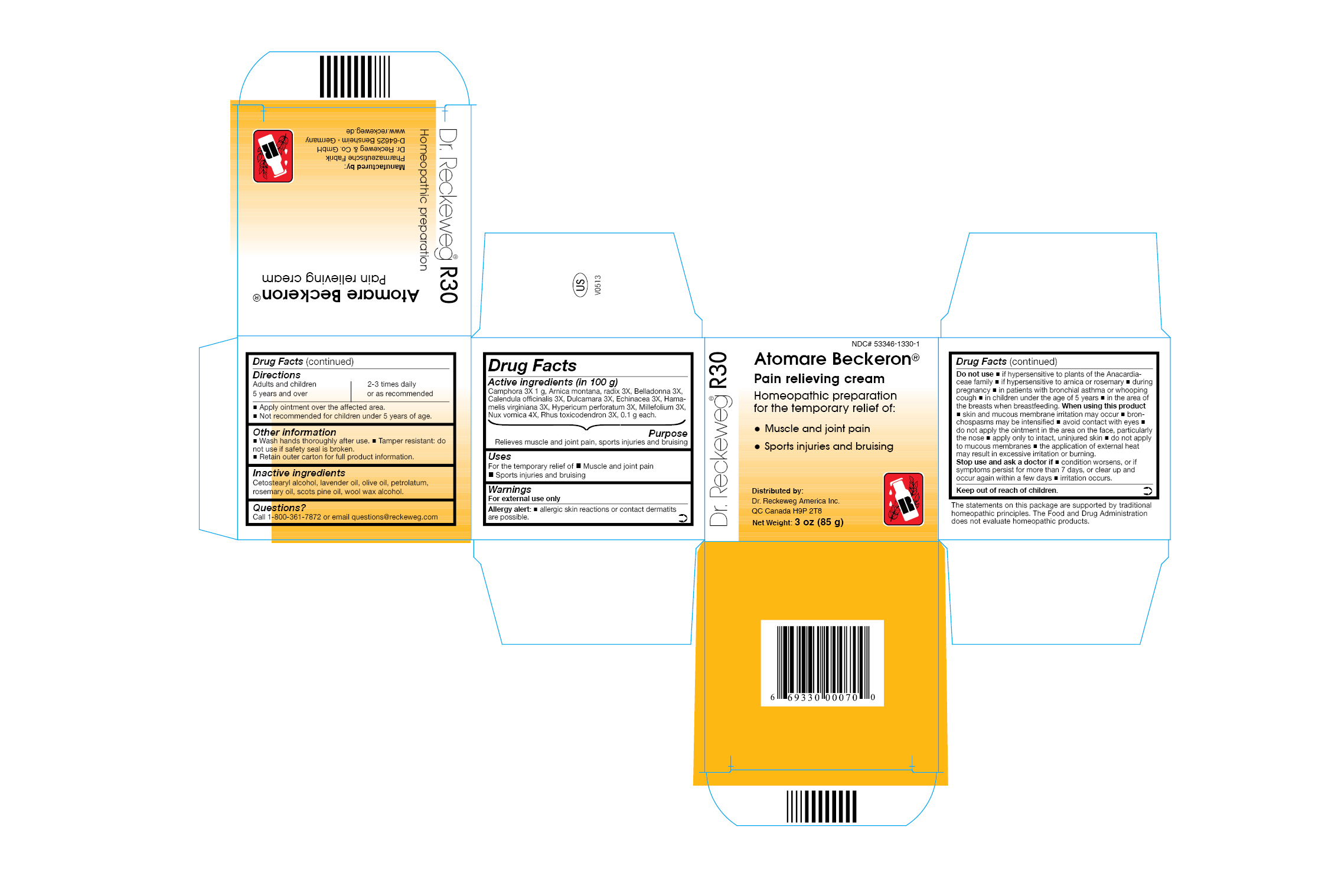 DRUG LABEL: DR. RECKEWEG R30 Atomare Beckeron
NDC: 53346-1330 | Form: OINTMENT
Manufacturer: PHARMAZEUTISCHE FABRIK DR. RECKEWEG & CO
Category: homeopathic | Type: HUMAN OTC DRUG LABEL
Date: 20130409

ACTIVE INGREDIENTS: CAMPHOR (NATURAL) 3 [hp_X]/85 g; ARNICA MONTANA ROOT 3 [hp_X]/85 g; ATROPA BELLADONNA 3 [hp_X]/85 g; CALENDULA OFFICINALIS FLOWERING TOP 3 [hp_X]/85 g; SOLANUM DULCAMARA TOP 3 [hp_X]/85 g; ECHINACEA, UNSPECIFIED 3 [hp_X]/85 g; HAMAMELIS VIRGINIANA ROOT BARK/STEM BARK  3 [hp_X]/85 g; HYPERICUM PERFORATUM 3 [hp_X]/85 g; ACHILLEA MILLEFOLIUM 3 [hp_X]/85 g; STRYCHNOS NUX-VOMICA SEED 4 [hp_X]/85 g; TOXICODENDRON PUBESCENS LEAF 3 [hp_X]/85 g
INACTIVE INGREDIENTS: CETOSTEARYL ALCOHOL; LAVENDER OIL; OLIVE OIL; PETROLATUM; ROSEMARY OIL; PINE NEEDLE OIL (PINUS SYLVESTRIS); LANOLIN ALCOHOLS

DR. RECKEWEG R30 Atomare Beckeron

Active ingredients

Camphora 3X 1 g, Arnica montana, radix 3X, Belladonna 3X, Calendula officinalis 3X, Dulcamara 3X, Echinacea 3X, Hamamelis virginiana 3X, Hypericum perforatum 3X, Millefolium 3X, Nux vomica 4X, Rhus tocicodendron 3X, 0.1 g each, in 100 g.

Purpose

Relieves muscle and joint pain, sports injuries and bruising

Uses

For the temporary relief of:

- Muscle and joint pain
- Sports injuries and bruising

Warnings

For external use only

Allergy alert:

- allergic skin reactions or contact dermatitis are possible.

Do not use

- if hypersensitive to plants of the Anacardiaceae family
- if hypersensitive to arnica or rosemary
- during pregnancy
- in patients with bronchial asthma or whooping cough
- in children under the age of 5 years
- in the area of the breasts when breastfeeding

When using this product

- skin and mucous membrane irritation may occur
- bronchospasms may be intensified
- avoid contact with eyes
- do not apply the ointment in the area on the face, particularly the nose
- apply only to intact, uninjured skin
- do not apply to mucous membranes
- the application of external heat may result in excessive irritation or burning.

Stop use and ask a doctor if

- condition worsens, or if symptoms persist for more than 7 days, or clear up and occur again within a few days
- irritation occurs.

Keep out of reach of children.

Directions
Adults and children ≥ 5 years: apply ointment over the affected area 2-3 times daily, or as recommended.

Not recommended for children under 5 years of age.

Other information

- Wash hands thoroughly after use.
- Tamper resistant: do not use if safety seal is broken.
- Retain outer carton for full product information.

Inactive ingredients

Cetostearyl alcohol, lavender oil, olive oil, petrolatum, rosemary oil, scots pine oil, wool wax alcohol.

Questions?

Call 1-800-361-7872 or email questions@reckeweg.com

PACKAGE LABEL

NDC# 53346-1330-1

DR. RECKEWEG R30 Atomare Beckeron

Pain relieving cream

Homeopathic preparation for the temporary relief of:

- muscle and joint pain
- sports injuries and bruising.

Manufactured by:

Pharmazeutische Fabrik Dr. Reckeweg Co. GmbH

D-64625 Bensheim

Germany

www.reckeweg.de

Net Weight: 3 oz (85 g)